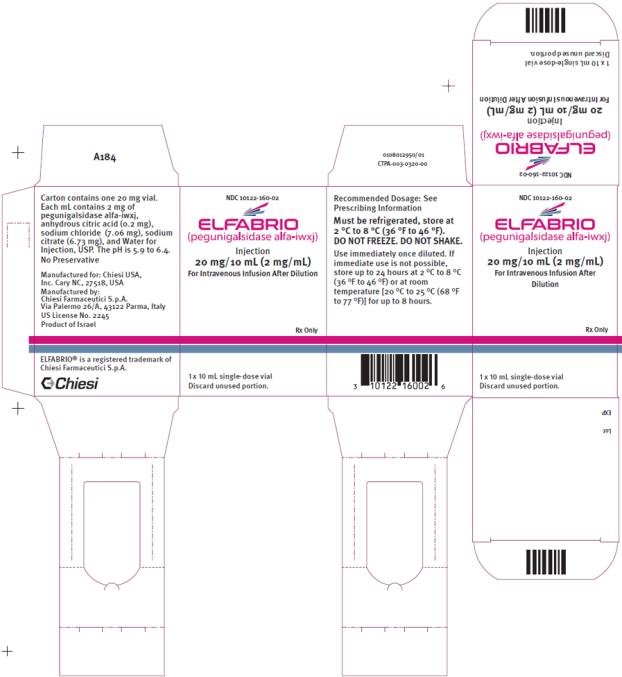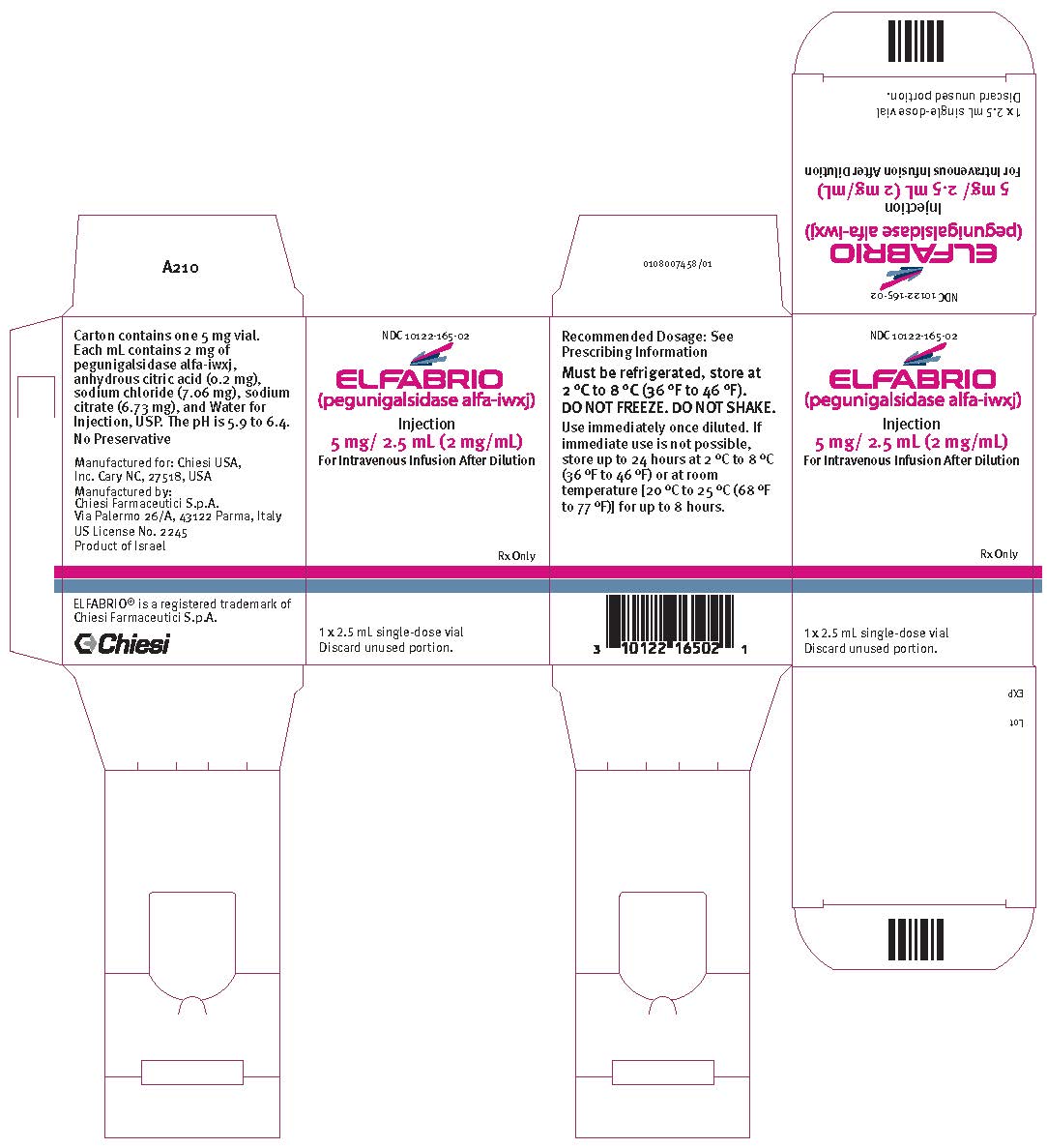 DRUG LABEL: ELFABRIO
NDC: 10122-160 | Form: INJECTION, SOLUTION, CONCENTRATE
Manufacturer: Chiesi USA, Inc.
Category: prescription | Type: HUMAN PRESCRIPTION DRUG LABEL
Date: 20240708

ACTIVE INGREDIENTS: PEGUNIGALSIDASE ALFA 20 mg/10 mL
INACTIVE INGREDIENTS: ANHYDROUS CITRIC ACID 2.0 mg/10 mL; SODIUM CHLORIDE 70.6 mg/10 mL; TRISODIUM CITRATE DIHYDRATE 76.7 mg/10 mL; WATER 9916.7 mg/10 mL

HIGHLIGHTS OF PRESCRIBING INFORMATION

These highlights do not include all the information needed to use ELFABRIO® safely and effectively. See full prescribing information for ELFABRIO.
ELFABRIO (pegunigalsidase alfa-iwxj) injection, for intravenous use
Initial U.S. Approval: 2023

WARNING: HYPERSENSITIVITY REACTIONS INCLUDING ANAPHYLAXIS

See full prescribing information for complete boxed warning.

Appropriate medical support measures, including cardiopulmonary resuscitation equipment, should be readily available. If a severe hypersensitivity reaction occurs, discontinue ELFABRIO immediately and initiate appropriate medical treatment. (5.1)

1 INDICATIONS AND USAGE

ELFABRIO is a hydrolytic lysosomal neutral glycosphingolipid-specific enzyme indicated for the treatment of adults with confirmed Fabry disease. (1)

2 DOSAGE AND ADMINISTRATION

- For pretreatment recommendations, see Full Prescribing Information. (2.1)
- Recommended dosage is 1 mg/kg every 2 weeks administered as an intravenous infusion. (2.2)
- For dosage and administration modifications due to hypersensitivity reactions or infusion-associated reactions (IARs), see Full Prescribing Information. (2.3)
- For instructions on preparation (including dilution), storage, and administration (including rates for the initial 4-6 infusions for ERT-experienced and ERT-naïve patients), see Full Prescribing Information. (2.4, 2.5, 2.6)

3 DOSAGE FORMS AND STRENGTHS

Injection: 20 mg/10 mL or 5 mg/2.5 mL (2 mg/mL) solution in a single-dose vial. (3)

4 CONTRAINDICATIONS

None. (4)

5 WARNINGS AND PRECAUTIONS

- Infusion-Associated Reactions: If severe IARs occur, discontinue ELFABRIO and initiate appropriate medical treatment. (5.2)
- Membranoproliferative Glomerulonephritis: Monitor serum creatinine and urinary protein to creatinine ratio. Discontinue ELFABRIO if glomerulonephritis is suspected, until a diagnostic evaluation can be conducted. (5.3)

6 ADVERSE REACTIONS

Most common adverse reactions (≥15%) are: infusion-associated reactions, nasopharyngitis, headache, diarrhea, fatigue, nausea, back pain, pain in extremity, and sinusitis. (6.1)

To report SUSPECTED ADVERSE REACTIONS, contact Chiesi USA, Inc. at 1-888-661-9260 or FDA at 1-800-FDA-1088 or www.fda.gov/medwatch.

FULL PRESCRIBING INFORMATION

WARNING: HYPERSENSITIVITY REACTIONS INCLUDING ANAPHYLAXIS

Patients treated with ELFABRIO have experienced hypersensitivity reactions, including anaphylaxis. Appropriate medical support measures, including cardiopulmonary resuscitation equipment, should be readily available during ELFABRIO administration. If a severe hypersensitivity reaction (e.g., anaphylaxis) occurs, discontinue ELFABRIO immediately and initiate appropriate medical treatment. In patients with severe hypersensitivity reaction, a desensitization procedure to ELFABRIO may be considered [see Warnings and Precautions (5.1)].

1 INDICATIONS AND USAGE

ELFABRIO is indicated for the treatment of adults with confirmed Fabry disease.

2 DOSAGE AND ADMINISTRATION

2.1 Recommendations Prior to ELFABRIO Treatment

Pretreatment

- In enzyme replacement therapy (ERT)-experienced patients, if pretreatment with antihistamines, antipyretics, and/or corticosteroids was used prior to ERT administration, consider similar pretreatment with these medications before the first several ELFABRIO infusions. After 4 to 6 ELFABRIO infusions, a stepwise decrease in the pretreatment medication dose(s) and/or discontinuation of the pretreatment medication(s) may be considered if treatment with ELFABRIO was tolerated.
- In ERT-naïve patients, prior to ELFABRIO administration, pre-treating with antihistamines, antipyretics, and/or corticosteroids may be considered [see Warnings and Precautions (5.1, 5.2)].

Medical Support

Appropriate medical support measures including cardiopulmonary resuscitation equipment should be readily available during ELFABRIO administration.

2.2 Recommended Dosage and Administration

The recommended dosage of ELFABRIO, based on actual body weight, is 1 mg/kg administered by intravenous infusion every 2 weeks.

The initial recommended ELFABRIO infusion rates for ERT-experienced or ERT-naïve patients are based on actual body weight [see Tables 1 and 2].

If one or more doses are missed, restart ELFABRIO treatment as soon as possible, maintaining the 2 week interval between infusions thereafter. Do not double a dose to compensate for a missed dose.

2.3 Administration Modifications Due to Hypersensitivity Reactions and/or Infusion-Associated Reactions

In the event of a severe hypersensitivity reaction (e.g., anaphylaxis) or severe infusion-associated reaction (IAR), immediately discontinue ELFABRIO administration and initiate appropriate medical treatment. For additional recommendations in the event of a severe hypersensitivity reaction or IAR, see Warnings and Precautions (5.1, 5.2).

In the event of a mild to moderate hypersensitivity reaction or a mild to moderate IAR, consider temporarily holding the infusion for 15 to 30 minutes or slowing the infusion rate by 25% to 50% [see Dosage and Administration (2.6)], and initiating appropriate medical treatment [see Warnings and Precautions (5.1, 5.2)].

- If symptoms persist despite holding or slowing the infusion, stop the infusion and monitor the patient. Consider re-initiating the infusion within 7 to 14 days at 25% to 50% of the rate at which the reaction occurred with appropriate pretreatment.
- If symptoms subside after holding the infusion, resume infusion at a 25% to 50% reduced rate as tolerated. Alternatively, if symptoms subside after slowing the infusion, complete infusion at the reduced rate as tolerated.
- Starting with the next infusion, increase the infusion rate by increments of 25% every third infusion as tolerated until the infusion rate at which the reaction occurred is reached. Closely monitor the patient.

2.4 Preparation Instructions

Use aseptic technique during preparation. Dilute ELFABRIO in the following manner:

- Determine the number of ELFABRIO vials to be diluted based on actual body weight in kg and the recommended dose [see Dosage and Administration (2.2) and Dosage Forms and Strengths (3)]. Round the number of vials up to the next whole number.
- Remove the appropriate number of ELFABRIO vials from the refrigerator and allow the vials to sit for 15-30 minutes at room temperature 20°C to 25°C (68°F to 77°F) before use. Do not use an external heat source to heat the product because heat may damage the product.
- Visually inspect the solution in the vials for particulate matter and discoloration. The solution should be clear and colorless. Discard if the solution is discolored or if visible particulate matter is present.
- Dilute the supplied ELFABRIO solution required for a dose in 0.9% Sodium Chloride Injection to a total volume based on actual body weight specified in Tables 1 and 2 below.
- Prior to adding the volume of ELFABRIO required for the dose, remove the equal volume of 0.9% Sodium Chloride Injection from the infusion bag.
- Withdraw the volume of ELFABRIO required for the dose from the vials (discard any unused solution remaining in the vial).
- Inject the ELFABRIO solution directly into the 0.9% Sodium Chloride Injection solution through the port of the infusion bag. Do not inject in the airspace within the infusion bag.
- Gently invert infusion bag to mix the solution. Avoid vigorous shaking or agitation.

2.5 Storage of the Diluted Solution

- If the diluted ELFABRIO solution is not used immediately:
  ○ Refrigerate the diluted solution at 2°C to 8°C (36°F to 46°F) for up to 24 hours. The solution must be infused within 8 hours after removal from the refrigerator, inclusive of the total infusion time, or discarded.
  ○ Store the diluted solution at room temperature at 20°C to 25°C (68°F to 77°F) for up to 8 hours. The solution must be used within 8 hours, inclusive of infusion time, or discarded.
- Do not freeze or shake.

2.6 Administration Instructions

Administer ELFABRIO as follows:

- Use an in-line low protein-binding, 0.2 micron, in-line filter during administration.
- For the initial 4-6 infusions, infuse ELFABRIO using the infusion rates described in Table 1 for ERT-experienced patients and Table 2 for ERT-naïve patients.
- If a patient tolerates the initial 4-6 ELFABRIO infusions, the duration of every third infusion may be decreased in decrements of 30 minutes as tolerated. The minimum recommended infusion duration is 1.5 hours.
- At the end of the infusion, flush the line with 0.9% Sodium Chloride Injection using the same infusion rate as the one used for the last part of the ELFABRIO infusion.
- Do not infuse ELFABRIO in the same intravenous line with other products.

Table 1 presents the recommended infusion rates for the initial 4-6 ELFABRIO infusions based on actual body weight for ERT-experienced patients.

Table 1: Recommended Infusion Rate^1 for ERT-Experienced Patients for the Initial 4-6 ELFABRIO Intravenous Infusions Based on Actual Body Weight
Actual Body Weight | Total Infusion Volume | Infusion Rate^1
˂ 70 kg | 150 mL | 0.83 mL/min (50 mL/h)
70 -100 kg | 250 mL | 1.39 mL/min (83 mL/h)
> 100 kg | 500 mL | 2.78 mL/min (167 mL/h)

^1 Infusion rate may be increased if the patient tolerates the initial 4-6 infusions (see above). Infusion rate may be slowed in case of a hypersensitivity reaction or an IAR [see Dosage and Administration (2.3)].

Table 2 presents the recommended infusion rates for the initial 4-6 ELFABRIO infusions based on actual body weight for ERT-naïve patients.

Table 2: Recommended Infusion Rate^1 for ERT-Naïve Patients for the Initial 4-6 ELFABRIO Intravenous Infusions Based on Actual Body Weight
Actual Body Weight | Total Infusion Volume | Infusion Rate^1
˂ 70 kg | 150 mL | 0.63 mL/min (37.5 mL/h)
70 -100 kg | 250 mL | 1 mL/min (60 mL/h)
> 100 kg | 500 mL | 1.38 mL/min (83 mL/h)

^1 Infusion rate may be increased if the patient tolerates the initial 4-6 infusions (see above). Infusion rate may be slowed in case of a hypersensitivity reaction or an IAR [see Dosage and Administration (2.3)].

Administration of ELFABRIO to Patients Previously Treated with ERT with an Infusion Duration Over 3 Hours

In patients previously treated with an ERT with an infusion duration over 3 hours:

- Use the same infusion rate for the ELFABRIO infusion.
- May decrease the duration of every third infusion after the initial 4-6 ELFABRIO infusions in decrements of 30 minutes as tolerated. The recommended minimum infusion duration of the maintenance infusion is 1.5 hours.

Home Infusion

Home administration under the supervision of a healthcare provider may be considered for patients who have reached an infusion duration that is tolerated well [see Dosage and Administration (2.1, 2.3)]. The decision to have a patient move to home infusion should be made after evaluation and recommendation by a healthcare provider.

The infusion duration should remain constant for home administration and the duration should only be decreased in a healthcare facility. In case of a missed dose or delayed infusion, a healthcare provider should be contacted.

3 DOSAGE FORMS AND STRENGTHS

Injection: 20 mg/10 mL or 5 mg/2.5 mL (2 mg/mL) of pegunigalsidase alfa-iwxj in a clear and colorless solution in a single-dose vial.

4 CONTRAINDICATIONS

None.

5 WARNINGS AND PRECAUTIONS

5.1 Hypersensitivity Reactions Including Anaphylaxis

Hypersensitivity reactions including anaphylaxis have been reported in ELFABRIO-treated patients. In clinical trials, 20 (14%) of ELFABRIO-treated patients experienced hypersensitivity reactions. In these trials, 4 ELFABRIO-treated patients (3%; 1 naïve to enzyme replacement therapy (ERT) and 3 ERT-experienced patients) experienced anaphylaxis during the initial infusion and were positive for anti-pegunigalsidase alfa-iwxj IgE antibodies (referred to as IgE ADA) [see Adverse Reactions (6.16.1) and Clinical Pharmacology (12.6)]. The risk of pegunigalsidase alfa-iwxj-related hypersensitivity may be increased in certain patients with pre-existing ADA from prior ERT [see Use In Specific Populations (8.6)].

Anaphylaxis (reported as Type I hypersensitivity reaction, hypersensitivity reaction, or bronchospasm) occurred within 5 to 40 minutes of the start of the initial infusion. Signs and symptoms included headache, nausea, vomiting, throat tightness, facial and oral edema, truncal rash, tachycardia, hypotension, rigors, urticaria, intense pruritus, moderate upper airway obstructions, macroglossia, and mild lip edema. Patients received treatment that included epinephrine, antihistamines and/or systemic corticosteroids.

Prior to ELFABRIO administration, consider pretreating with antihistamines, antipyretics, and/or corticosteroids. Appropriate medical support measures, including cardiopulmonary resuscitation equipment, should be readily available during ELFABRIO administration.

- If a severe hypersensitivity reaction (e.g., anaphylaxis) occurs, discontinue ELFABRIO immediately and initiate appropriate medical treatment. Consider the risks and benefits of re-administering ELFABRIO following severe hypersensitivity reactions (including anaphylaxis). Patients may be rechallenged using slower infusion rates. In patients with severe hypersensitivity reaction, desensitization measures to ELFABRIO may be considered. If the decision is made to readminister ELFABRIO, ensure the patient tolerates the infusion. If the patient tolerates the infusion, the rate may be increased to reach the recommended rate.
- If a mild or moderate hypersensitivity reaction occurs, consider temporarily holding the infusion or slowing the infusion rate [see Dosage and Administration (2.3)].

Consider monitoring patients who demonstrate hypersensitivity reactions during ELFABRIO treatment for the presence of IgG and IgE ADA [see Clinical Pharmacology (12.6)].

5.2 Infusion-Associated Reactions

Infusion-associated reactions (IARs) have been reported in ELFABRIO-treated patients. In clinical trials, 41 (29%) of ELFABRIO-treated patients experienced one or more IARs, defined as any adverse reaction with onset after start of the infusion and up to 24 hours after the end of infusion. The risk of pegunigalsidase alfa-iwxj-related IARs may be increased in certain patients with pre-existing ADA from prior ERT [see Use In Specific Populations (8.6)].

IARs included anaphylaxis reactions during the initial ELFABRIO administration [see Warnings and Precautions (5.1)].

In addition to the hypersensitivity reactions described above [see Warnings and Precautions (5.1)], other IARs included nausea, chills, pruritus, rash, chest pain, dizziness, vomiting, asthenia, pain, sneezing, dyspnea, nasal congestion, throat irritation, abdominal pain, erythema, diarrhea, burning sensation, neuralgia, headache, paresthesia, tremor, agitation, increased body temperature, flushing, bradycardia, myalgia, hypertension, and hypotension [see Adverse Reactions (6.1)].

Up to 40% of patients were pretreated with diphenhydramine, prednisone and/or acetaminophen at least once during the clinical trials. Severe reactions in the trials were generally managed with administration of antipyretics, antihistamines, corticosteroids, intravenous fluids, and/or oxygen.

IARs were more frequently observed in ELFABRIO-treated patients who developed IgG anti-drug antibodies (ADA) including patients who had pre-existing IgG ADA [see Adverse Reactions (6.16.1) and Clinical Pharmacology (12.6)]. Consider monitoring patients who demonstrate IARs during ELFABRIO treatment for the presence of IgG and IgE ADA.

Patients with advanced Fabry disease may have compromised cardiac function which may predispose them to a higher risk of severe complications from IARs. Closely monitor patients with compromised cardiac function if ELFABRIO is administered to these patients.

Prior to ELFABRIO administration, consider pre-treating with antihistamines, antipyretics, and/or corticosteroids to reduce the risk of IARs. However, IARs may still occur in patients after receiving pre-treatment.

- If a severe IAR occurs, discontinue ELFABRIO immediately and initiate appropriate medical treatment. Consider the risks and benefits of re-administering ELFABRIO following a severe IAR. Patients may be rechallenged using slower infusion rates. Once a patient tolerates the infusion, the infusion rate may be increased to reach the recommended infusion rate.
- If a mild or moderate IAR occurs, consider temporarily holding the infusion or slowing the infusion rate [see Dosage and Administration (2.3)].

5.3 Membranoproliferative Glomerulonephritis

A case of membranoproliferative glomerulonephritis with immune depositions in the kidney was reported during clinical trials [see Adverse Reactions (6.1)]. This event led to a decline in renal function that slowly improved upon discontinuation of ELFABRIO but did not return to baseline by the end of the trial. Monitor serum creatinine and urinary protein to creatinine ratio. If glomerulonephritis is suspected, discontinue ELFABRIO until a diagnostic evaluation can be conducted.

6 ADVERSE REACTIONS

The following clinically significant adverse reactions are described elsewhere in labeling:

- Hypersensitivity Reactions Including Anaphylaxis [see Warnings and Precautions (5.1)]
- Infusion-Associated Reactions (IARs) [see Warnings and Precautions (5.2)]
- Membranoproliferative Glomerulonephritis [see Warnings and Precautions (5.3)]

6.1 Clinical Trials Experience

Because clinical trials are conducted under widely varying conditions, adverse reaction rates observed in the clinical trials of a drug cannot be directly compared to rates in the clinical trial of another drug and may not reflect the rates observed in clinical practice.

Adverse Reactions From Trial 2

The safety of ELFABRIO in adults with confirmed Fabry disease who had been previously treated with agalsidase beta was evaluated in Trial 2 which included a total of 52 ELFABRIO-treated patients (29 male, 23 female aged 20 to 60 years old) with Fabry disease [see Clinical Studies (14)]. Patients received 1 mg/kg of ELFABRIO given intravenously every 2 weeks for at least 104 weeks.

The most common adverse reactions (≥15%) reported with ELFABRIO were infusion-associated reactions which occurred in 17 patients (32%); followed by, nasopharyngitis and headache each in 11 patients (21%); diarrhea in 10 patients (19%); fatigue and nausea each in 9 patients (17%); and back pain, pain in extremity, and sinusitis each in 8 patients (15%).

One ELFABRIO-treated patient experienced a severe hypersensitivity reaction during the first infusion. The patient withdrew from the trial following a moderate hypersensitivity reaction during the second infusion.

Table 3 lists adverse reactions reported in at least 5% of ELFABRIO-treated patients in Trial 2.

Table 3: Adverse Reactions in Adults With Fabry Disease (Trial 2)^1
Adverse Reaction | ELFABRIO N=52 n (%) | Agalsidase beta N=25 n (%)
Infusion-Associated Reaction^2,4 | 17 (32) | 8 (32)
Nasopharyngitis | 11 (21) | 4 (16)
Headache | 11 (21) | 5 (20)
Diarrhea | 10 (19) | 6 (24)
Fatigue | 9 (17) | 4 (16)
Nausea | 9 (17) | 3 (12)
Back pain | 8 (15) | 5 (20)
Pain in Extremity | 8 (15) | 4 (16)
Sinusitis | 8 (15) | 3 (12)
Abdominal Pain | 6 (12) | 0 (0)
Proteinuria | 6 (12) | 0 (0)
Hypersensitivity^3,4 | 5 (9) | 4 (16)
Upper Respiratory Tract Congestion | 4 (8) | 0 (0)
Neuralgia | 4 (8) | 0 (0)
Peripheral Neuropathy | 3 (6) | 0 (0)
Sciatica | 3 (6) | 0 (0)
Infusion Site Extravasation | 3 (6) | 0 (0)
Hematuria | 3 (6) | 0 (0)

^1 Adverse reactions were those that occurred in ≥ 5% of ELFABRIO-treated patients.
^2 “Infusion-associated reaction” includes nausea, vomiting, abdominal pain, diarrhea, fatigue, chills, malaise, non-cardiac chest pain, hypersensitivity, body temperature increased, burning sensation, neuralgia, agitation, throat irritation, pruritic rash, and flushing. Events occurring within 24 hours.
^3 “Hypersensitivity” includes macular rash, pruritic rash, and face swelling. Events occurring within 24 hours.
^4 The events of hypersensitivity and pruritic rash fall in both hypersensitivity and IAR categories.

Membranoproliferative Glomerulonephritis

A case of membranoproliferative glomerulonephritis with immune depositions in the kidney was reported in an ELFABRIO-treated patient.

Immunogenicity: Anti-Drug Antibody-Associated Adverse Reactions

Of the patients who experienced serious hypersensitivity reactions during the first ELFABRIO infusion and had pre-infusion samples and samples available for testing at the time of the event, all but one had pre-existing IgE ADAs and all tested positive for IgE ADAs at the time of the reaction.

In the overall clinical program, IARs occurred in 51% (19/37) of patients who were IgG ADA positive at baseline compared to 16% (13/84) in IgG ADA negative patients [see Clinical Pharmacology (12.6)].

8 USE IN SPECIFIC POPULATIONS

8.1 Pregnancy

Risk Summary

There are no available data on ELFABRIO use in pregnant females to evaluate a drug-associated risk of major birth defects, miscarriage or other adverse maternal or fetal outcomes; however, as an enzyme replacement, ELFABRIO is not expected to cause adverse outcomes. Animal reproduction studies have been conducted with pegunigalsidase alfa-iwxj in pregnant rats and rabbits. No adverse effects on embryofetal development were observed in pregnant rats intravenously administered pegunigalsidase alfa-iwxj twice per week at exposures up to 3.6 times that of the maximum recommended human dose (MRHD) (based on area under the concentration-time curve (AUC)). Maternal toxicity was observed in pregnant rabbits intravenously administered pegunigalsidase alfa-iwxj twice per week at doses that were ≥ 3.2 times the MRHD (based on human equivalent dose) [see Data].

The estimated background risk of major birth defects and miscarriage in the indicated population is unknown. All pregnancies have a background risk of birth defect, loss or other adverse outcomes. In the U.S. general population, the estimated background risk of major birth defects and miscarriage in clinically recognized pregnancies is 2% to 4% and 15% to 20%, respectively.

There is a pregnancy safety study for ELFABRIO. If a patient becomes pregnant while receiving ELFABRIO, healthcare providers should report ELFABRIO exposure by calling 1-888-661-9260 or visiting https://chiesirarediseases.com/contact-us/medical-information-form.

Data

Animal Data

In an embryofetal development study in the rat, pegunigalsidase alfa-iwxj was administered during the period of organogenesis on gestation day 6, 9, 12, and 15. No maternal or fetal adverse effects were noted at exposures that were up to 3.6-fold greater than the recommended dose of 1 mg/kg every two weeks.

In an embryofetal development study in the rabbit, administration of pegunigalsidase alfa-iwxj during the period of organogenesis on gestation day 6, 9, 12, 15, and 18, resulted in maternal toxicity, including maternal mortality, decreased body weight, and decreased feed consumption. These effects were observed at exposures that were ≥ 3.2-fold greater than the recommended dose of 1 mg/kg every two weeks. Adverse embryofetal effects included abortion, increased late resorptions, number of does with resorptions, and increased post-implantation loss at exposures that were 6.5 fold greater than the recommended dose of 1 mg/kg every two weeks. Decreased fetal body weight was observed at exposures that were ≥ 3.2 times greater than the recommended dose of 1 mg/kg every two weeks. There was no increase in fetal external, skeletal, or visceral malformations.

8.2 Lactation

Risk Summary

There are no data on the presence of pegunigalsidase alfa-iwxj in either human or animal milk, the effects on the breastfed infant, or the effects on milk production. The developmental and health benefits of breastfeeding should be considered along with the mother’s clinical need for ELFABRIO and any potential adverse effects on the breastfed infant from pegunigalsidase alfa-iwxj or from the underlying maternal condition.

8.4 Pediatric Use

The safety and effectiveness of ELFABRIO have not been established in pediatric patients.

8.5 Geriatric Use

Clinical trials of ELFABRIO did not include patients 65 years of age and older to determine if they respond differently from younger adult patients.

8.6 Patients with Prior Enzyme Replacement Therapy

Patients that received prior ERT are more likely to have pre-existing anti-drug antibodies (ADA) to pegunigalsidase alfa-iwxj which could be due to the ADA cross-reactivity to pegunigalsidase alfa-iwxj by prior ERT. When switching from other ERT to ELFABRIO:

- Pre-existing ADA may reduce the plasma pegunigalsidase alfa-iwxj concentrations, which may reduce ELFABRIO efficacy [see Clinical Pharmacology (12.2, 12.6)].
- The risk of ELFABRIO-related hypersensitivity and infusion-associated reactions may be increased in certain patients with pre-existing ADA from prior ERT [see Warnings and Precautions (5.1, 5.2) and Adverse Reactions (6.1)].

Consider monitoring clinical or pharmacodynamic responses (e.g., plasma lyso-Gb3 levels) when switching from agalsidase beta to ELFABRIO, in patients with pre-existing ADA.

11 DESCRIPTION

Pegunigalsidase alfa-iwxj, a hydrolytic lysosomal neutral glycosphingolipid-specific enzyme, is a PEGylated and crosslinked, chemically modified, recombinant human alpha-galactosidase A enzyme that is produced by genetically modified Bright Yellow 2 (Nicotiana tabacum) plant cells. The amino acid sequence of one subunit of pegunigalsidase alfa-iwxj consists of 405 amino acids, of which 398 amino acids are identical to human alpha-GAL-A with an additional 6 amino acids (SEKDEL) included at the C-terminal to encode an endoplasmic retrieval signal, and an additional glycine at the N-terminus derived from the signal peptide.

Pegunigalsidase alfa-iwxj is a homodimeric glycoprotein covalently crosslinked with an average of nine 2.3 kDa PEG per dimer. The total molecular weight of the cross-linked dimer is approximately 116 kDa. Pegunigalsidase alfa-iwxj has specific activity of approximately 35-62 U/mg (one enzyme unit is defined as the amount of enzyme which catalyzes the hydrolysis of one micromole of synthetic substrate, p-nitrophenyl-α-D-galactopyranoside per minute at 37°C).

ELFABRIO (pegunigalsidase alfa-iwxj) injection is a sterile, preservative-free, 20 mg/10 mL or 5 mg/2.5 mL (2 mg/mL) solution in a single-dose vial for intravenous infusion after dilution. Each mL contains 2 mg of pegunigalsidase alfa-iwxj, anhydrous citric acid (0.2 mg), sodium chloride (7.06 mg), sodium citrate (6.73 mg), and Water for Injection, USP. The pH is approximately 5.9 to 6.4.

12 CLINICAL PHARMACOLOGY

12.1 Mechanism of Action

Fabry disease is caused by deficiency of the lysosomal enzyme alpha-galactosidase A. ELFABRIO provides an exogenous source of alpha-galactosidase A. ELFABRIO is internalized and transported into lysosomes where it is thought to exert enzymatic activity and reduce accumulated globotriaosylceramide (Gb3).

12.2 Pharmacodynamics

Plasma globotriaosylsphingosine (lyso-Gb3, a metabolite of Gb3) concentrations are elevated in patients with Fabry disease. In patients with Fabry disease who were [see Clinical Studies (14)]:

- ERT-naïve or had not received ERT treatment for at least 26 weeks and had a negative test for anti-pegunigalsidase alfa-iwxj antibodies (Trial 1), ELFABRIO treatment resulted in significant reductions in median plasma lyso-Gb3 concentrations compared to baseline of approximately:
  ○ -43% (Week 4), -57% (Week 26), -68% (Week 52), and -84% (Week 104) in male patients, and
  ○ -3% (Week 4), -19% (Week 26), -32% (Week 52), and -75% (Week 104) in female patients.
- ERT-experienced for at least 104 weeks (Trial 2), switching to ELFABRIO treatment resulted in increases in median plasma lyso-Gb3 concentrations compared to baseline of:
  ○ Approximately 11% (Week 6), 15% (Week 26), and 18% (Week 104) in male patients, and
  ○ No significant changes in median plasma lyso-Gb3 concentrations in female patients.

Pegunigalsidase alfa-iwxj exposure-response relationship is unknown.

12.3 Pharmacokinetics

The pharmacokinetics (PK) of pegunigalsidase alfa-iwxj were evaluated in adult patients with Fabry disease and are presented as mean (standard deviation, SD) unless otherwise specified. The pharmacokinetics of pegunigalsidase alfa-iwxj in plasma following intravenous infusion of ELFABRIO 1 mg/kg every 2 weeks in adult treatment-naïve patients with Fabry disease are summarized in Table 4. The maximum plasma concentration (Cmax) and area under the concentration-time curve (AUC) of pegunigalsidase alfa-iwxj increased with longer duration of treatment. In adult ERT-experienced patients with Fabry disease, mean Cmax ranged from 21.2 to 23.3 μg/mL and mean AUCtau ranged from 958 to 1074 μg·h/mL following intravenous infusion of ELFABRIO 1 mg/kg every 2 weeks.

Table 4: Pharmacokinetics of Pegunigalsidase Alfa-iwxj in Adult ERT-Naïve^1 Patients With Fabry Disease Following Intravenous Infusion of ELFABRIO 1 mg/kg Every 2 Weeks
PK Parameters | Pegunigalsidase Alfa-iwxj
 | Day 1 | Week 13 | Week 26 | Week 52
Mean Infusion Duration (h) | 5.5 | 4.4 | 3.9 | 3.3
General Information
Cmax (μg/mL) | 11.1±2.4 | 11.9±2.4 | 13.3±3.0 | 17.3±6.1
AUCinf (μg·h/mL) | 391±136 | 510±174 | 748±200 | 1428±875
Distribution
V (mL/kg) | 321±71 | 271±89 | 226±116 | 186±91
Elimination
t1/2 (h) | 78.9±10.3 | 85.7±28.4 | 96.5±31.4 | 121±22
CL (mL/h/kg) | 2.9±0.7 | 2.3±0.8 | 1.6±0.6 | 1.1±0.7
Metabolism | Expected metabolism into small peptides by catabolic pathways

Cmax=maximum plasma concentration; AUC=area under the plasma concentration-time curve; V= terminal volume of distribution; t1/2=elimination half-life; CL=clearance
^1 Includes patients who had not received ERT for at least 26 Weeks and who tested negative for anti-pegunigalsidase alfa-iwxj antibodies at screening.

12.6 Immunogenicity

The observed incidence of IgG anti-drug antibodies (ADA) is highly dependent on the sensitivity and specificity of the assay. Differences in assay methods preclude meaningful comparisons of the incidence of ADA in the studies described below with the incidence of ADA in other studies, including those of pegunigalsidase alfa-iwxj ELFABRIO or of other pegunigalsidase alfa products.

The incidences of IgG ADA in ELFABRIO-treated patients with Fabry disease in Trials 1 and 2 are shown in Table 5.

Immunogenicity in ERT-Naïve Patients or Those Who Did Not Receive ERT for 26 Weeks

In Trial 1 (ERT-naïve patients with Fabry disease or those who did not receive ERT for 26 weeks) [see Clinical Studies (14)]:

- Four of the 14 ELFABRIO-treated who were IgG anti-pegunigalsidase alfa-iwxj antibodies (anti-drug antibodies or ADA) negative at baseline became ADA positive during ELFABRIO treatment. The onset of ADA positivity in 3 of these patients occurred within 26 weeks after starting ELFABRIO treatment.
- Two patients had ADA prior to receiving their first ELFABRIO dose. One of these patients remained ADA positive after receiving ELFABRIO treatment (this patient had boosted antibody titers during ELFABRIO treatment).

Immunogenicity in ERT-Experienced Patients

In Trial 2 (ERT-experienced patients with Fabry disease who switched from agalsidase beta [see Clinical Studies (14)]:

- Three of the 34 ELFABRIO-treated patients who were ADA negative at baseline became ADA positive during ELFABRIO treatment. The onset of ADA positivity occurred within 26 weeks after starting ELFABRIO treatment in 1 patient and more than 52 weeks in the remaining 2 patients.
- Eighteen ELFABRIO-treated patients had ADA prior to receiving their first ELFABRIO dose:
  ○ 17 (94%) patients remained ADA positive after receiving ELFABRIO treatment at 1 or more timepoints.
  ○ 3 (17%) patients had boosted ADA titers during ELFABRIO treatment.

Table 5: ADA Incidence in ELFABRIO-Treated Patients with Fabry Disease (Trials 1 and 2)
 | Trial 1 ERT-Naïve^1 Patients |  | Trial 2 ERT-Experienced Patients
Baseline
 | Male (N=11) | Female (N=7) | Male (N=29) | Female (N=23)
ADA | 1 (9%) | 1 (14%) | 18 (62%) | 0
Neutralizing antibody^2 | 0 | 0 | 17/18 | 0
Anti-enzyme antibody^3 | 1/1 | 1/1 | 18/18 | 0
Anti-PEG antibody^4 | 0 | 0 | 2/18 | 0
Anti-plant glycan antibody^5 | 1/1 | 1/1 | 0 | 0
At any time during ELFABRIO treatment*
 | Male (N=9) | Female (N=7) | Male (N=29) | Female (N=23)
ADA | 5 (56%) | 0 | 17 (59%) | 3 (13%)
Neutralizing antibody^2 | 3/5 | 0 | 14/17 | 1/3
Anti-enzyme antibody^3 | 4/5 | 0 | 17/17 | 1/3
Anti-PEG antibody^4 | 1/5 | 0 | 2/17 | 1/3
Anti-plant glycan antibody^5 | 2/5 | 0 | 0 | 0

ADA, anti-drug antibodies
*ADA incidence after ELFABRIO treatment was determined if positive at any timepoint during ELFABRIO treatment.
In Trial 1, of those that were positive at baseline (N=2) or any timepoint during ELFABRIO treatment (N=5), 4 became negative for ADA during Trial 1 through their last timepoint on study. In Trial 2, of those that were positive at baseline (N=18) or any timepoint during ELFABRIO treatment (N=20), 8 became negative for ADA during Trial 2 through their last timepoint on study.
^1 Includes patients who had not received ERT for at least 26 Weeks and who tested negative for anti-pegunigalsidase alfa-iwxj antibodies at screening.
^2Neutralizing antibodies that inhibit enzyme activity, tested for IgG ADA positive samples only. Assessments for neutralizing antibodies that inhibit cellular uptake of enzyme have not been performed.
^3 Anti-pegunigalsidase alfa-iwxj antibodies specific to the enzyme moiety on pegunigalsidase alfa-iwxj, tested for IgG ADA positive samples only
^4 Anti-pegunigalsidase alfa-iwxj antibodies specific to the PEG moieties on pegunigalsidase alfa-iwxj, tested for IgG ADA positive samples only
^5 Anti-pegunigalsidase alfa-iwxj antibodies specific to the plant glycan motifs on pegunigalsidase alfa-iwxj, tested for IgG ADA positive samples only

ADA Effects on Safety and Efficacy

IARs occurred more frequently in ELFABRIO-treated patients who were IgG ADA positive compared to those that were IgG ADA negative [see Warnings and Precautions (5.2) and Adverse Reactions (6.1)]. The effect of IgE ADA on hypersensitivity reactions of ELFABRIO treatment has not been fully characterized [see Warnings and Precautions (5.1)].

The effect of IgG ADA on the effectiveness of ELFABRIO has not been fully characterized [see Use in Specific Populations (8.6)].

ADA Effects on Pharmacodynamics

In Trial 2, baseline and post-treatment plasma lyso-Gb3 levels were higher in ELFABRIO-treated patients who were IgG ADA positive at baseline or at any time during the treatment compared with patients who were IgG ADA negative at baseline and at any time during the treatment [see Clinical Pharmacology (12.2)]. The IgG ADA positive patient who had plasma pegunigalsidase alfa-iwxj concentrations below the limit of quantification of the assay had the highest plasma lyso-Gb3 levels among ELFABRIO-treated patients.

ADA Effects on Pharmacokinetics

IgG ADA including pre-existing IgG ADA reduced plasma pegunigalsidase alfa-iwxj concentrations in ELFABRIO-treated patients with Fabry disease. Patients with higher ADA titers had lower pegunigalsidase alfa-iwxj concentrations compared to those with lower ADA titers.

In Trial 1 in patients who were negative for ADA at screening, 3 patients developed ADA following ELFABRIO treatment and had plasma pegunigalsidase alfa-iwxj concentration measures. Of these three patients:

- The plasma pegunigalsidase alfa-iwxj concentrations were transiently decreased in two of the patients who received 0.2 mg/kg of ELFABRIO intravenously every other week (0.2 times the approved recommended dosage), and
- No ADA effect on pegunigalsidase alfa-iwxj concentrations was observed in the third patient who received 1 mg/kg of ELFABRIO intravenously every other week.

In Trial 2, 3 of 17 patients who had plasma pegunigalsidase alfa-iwxj concentration measures had pre-existing ADA at baseline and maintained ADA positive status following ELFABRIO treatment [see Use in Specific Populations (8.6)]. Of these three patients:

- 1 patient with the highest ADA titer had plasma pegunigalsidase alfa-iwxj concentrations that were below the limit of quantification of the assay at all trial visits with pharmacokinetic assessments, and
- 2 patients had low plasma pegunigalsidase alfa-iwxj AUC, approximately 5% of the expected AUC for ADA-negative ELFABRIO-treated patients.

13 NONCLINICAL TOXICOLOGY

13.1 Carcinogenesis, Mutagenesis, Impairment of Fertility

Animal studies to evaluate the carcinogenic potential of pegunigalsidase alfa-iwxj have not been conducted. No effect on fertility was observed when pegunigalsidase alfa-iwxj was administered to adult rats at exposures ≤ 3.6-fold greater than the recommended dose of 1 mg/kg every two weeks.

14 CLINICAL STUDIES

Trial 1 was an open-label dose-ranging trial in adults diagnosed with Fabry disease (NCT01678898). Patients received ELFABRIO at 0.2 mg/kg, 1 mg/kg, or 2 mg/kg given intravenously every other week for 52 weeks. The 0.2 mg/kg and 2 mg/kg dosage regimens are not approved and are not recommended [see Dosage and Administration (2.2)].

Trial 1 enrolled 18 patients who were ERT-naïve or who had not received ERT for more than 26 weeks and had a negative test for anti-pegunigalsidase alfa-iwxj IgG antibodies prior to enrollment. Two patients in the 1 mg/kg treatment group discontinued the trial after their first infusion; one of them discontinued due to severe hypersensitivity reaction. Among the remaining 16 patients who completed Trial 1, 9 (56%) were males and 7 (44%) were females ranging in age from 17 to 54 years with a median age of 30 years. Twelve patients were White (75%) and 3 were Black or African American (19%). Three patients were Hispanic/Latino and 13 patients were not Hispanic/Latino. Of the 9 males, 7 (78%) had the classic phenotype. The median baseline eGFR and proteinuria was 115 mL/min/1.73 m^2 and 0.11 g/g respectively. Among the male patients, the median value of residual alpha-galactosidase A activity was 2.4% (range: 0.0%-9.3%) in plasma and 1.3% (range: 0.0%-3.4%) in leukocytes.

The average number of globotriaosylceramide (Gb3) inclusions per renal peritubular capillary (PTC) in renal biopsy specimens of patients was assessed by light microscopy using the quantitative Barisoni Lipid Inclusion Scoring System (BLISS). Evaluable renal biopsies were obtained at baseline and at 26 weeks of treatment in 14 of the 16 patients who completed Trial 1.

Table 6 shows the changes from baseline to 26 weeks in the BLISS score (average number of Gb3 inclusions per renal PTC) for these 14 ELFABRIO-treated patients.

Table 6: Summary of the Renal Biopsy BLISS Score^1 of Gb3 Inclusions at Baseline and after 26 Weeks of ELFABRIO Treatment in Adults with Fabry Disease (Trial 1)
 | All Patients | Males | Females
 | (N = 14) | (N = 8) | (N = 6)
Median (range)
Baseline | 3.2 (0.4, 9.0) | 6.8 (0.4, 9.0) | 1.2 (0.8, 3.3)
Week 26 | 0.7 (0.3, 2.5) | 0.7 (0.3, 2.5) | 0.7 (0.3, 1.4)
Change at Week 26 | -2.5 (-8.5, 0.5) | -5.3 (-8.5, 0.5) | -0.7 (-2.5, 0.1)
Mean Change at Week 26 (95% CI) | -3.1 (-4.8, -1.4) | -4.7 (-7.1, -2.3) | -1.0 (-2.1, 0.1)

^1 The BLISS methodology counts the number of Gb3 inclusions in each renal PTC contained in a biopsy specimen. For each biopsy specimen (slide), approximately 300 renal PTCs were scored, and the final biopsy score for each patient was determined as the average number of Gb3 inclusions per PTC.

Trial 2 was a randomized, double-blind, and active-controlled trial (NCT02795676) in ERT-experienced adults diagnosed with Fabry disease. Eligible patients were treated with agalsidase beta for at least one year prior to trial entry (the mean duration of agalsidase beta treatment prior to enrollment was 5.7 years). Patients were randomized 2:1 to receive ELFABRIO (1 mg/kg intravenous infusion) or agalsidase beta (1 mg/kg intravenous infusion) every 2 weeks for 104 weeks.

A total of 77 patients were randomized and received at least one dose of ELFABRIO (N = 52, 68%) or agalsidase beta (N = 25, 32%). Of these patients, 47 (61%) were males and 30 (39%) were females. Patients were 18 to 60 years of age with a median age of 46 years at baseline; 72 (94%) were White, 3 (4%) were Black or African American and 2 (3%) were Asian. Two patients were Hispanic/Latino and 75 patients were not Hispanic/Latino. Forty-one (53%) patients had the classic phenotype. The median baseline eGFR and proteinuria was 75 mL/min/1.73 m^2 and 0.11 g/g, respectively.

The primary efficacy endpoint was the annualized rate of change in eGFR (eGFR slope) assessed over 104 weeks. The estimated mean eGFR slope was -2.4 and -2.3 mL/min/1.73 m^2/year on ELFABRIO and agalsidase beta respectively. The estimated treatment difference was -0.1 (95% CI: -2.3, 2.1) mL/min/1.73 m^2/year.

16 HOW SUPPLIED/STORAGE AND HANDLING

How Supplied

ELFABRIO (pegunigalsidase alfa-iwxj) injection is a sterile, preservative-free, clear and colorless solution supplied in a single-dose vial. Each vial contains 20 mg/10 mL or 5 mg/2.5 mL (2 mg/mL) of pegunigalsidase alfa-iwxj. ELFABRIO is available as:

- One single-dose 20 mg/10 mLvial in a carton (NDC 10122-160-02)
- One single-dose 5 mg/2.5 mL vial in a carton (NDC 10122-165-02)
- Five single-dose 20 mg/10 mL vials in a carton (NDC 10122-160-05)
- Ten single-dose 20 mg/10 mL vials in a carton (NDC 10122-160-10)

Storage and Handling

Store refrigerated at 2°C to 8°C (36°F to 46°F). Do not freeze. Do not shake.

17 PATIENT COUNSELING INFORMATION

Hypersensitivity Reactions Including Anaphylaxis and Infusion-Associated Reactions (IARs)

Advise the patient and/or caregiver that reactions related to the infusion may occur during and after ELFABRIO treatment, including anaphylactic reactions, other serious or severe hypersensitivity reactions, and IARs. Inform the patient and/or caregiver of the signs and symptoms of hypersensitivity reactions and IARs and to seek immediate medical care should these signs and symptoms occur [see Warnings and Precautions (5.1, 5.2)].

Pregnancy Safety Study

Advise a patient who is exposed to ELFABRIO during pregnancy that there is a pregnancy safety study that monitors pregnancy outcomes. Encourage the patient to report the pregnancy to Chiesi USA, Inc. at 1-888-661-9260 and https://chiesirarediseases.com/contact-us/medical-information-form [see Use in Specific Populations (8.1)].

Manufactured by:
Chiesi Farmaceutici S.p.A.
Via Palermo 26/A, 43122 Parma, Italy
U.S. License No. 2245

Manufactured at:
Chiesi Farmaceutici S.p.A.
43122 Parma, Italy

Manufactured for:
Chiesi USA, Inc.
Cary NC, 27518, USA
Product of Israel.

ELFABRIO is a registered trademark of Chiesi Farmaceutici S.p.A.
Licensed from Protalix Ltd.
CTPA-001-0324-01-W

PRINCIPAL DISPLAY PANEL

NDC 10122-160-02
ELFABRIO
(pegunigalsidase alfa-iwxj)
Injection
20 mg/ 10 mL (2 mg/ml)
For Intravenous Infusion After Dilution
Rx Only
1 x 10 mL single-dose vial
Discard unused portion.

PRINCIPAL DISPLAY PANEL

NDC 10122-165-02
ELFABRIO
(pegunigalsidase alfa-iwxj)
Injection
5 mg/ 2.5 mL (2 mg/ml)
For Intravenous Infusion After Dilution
Rx Only
1 x 2.5 mL single-dose vial
Discard unused portion.